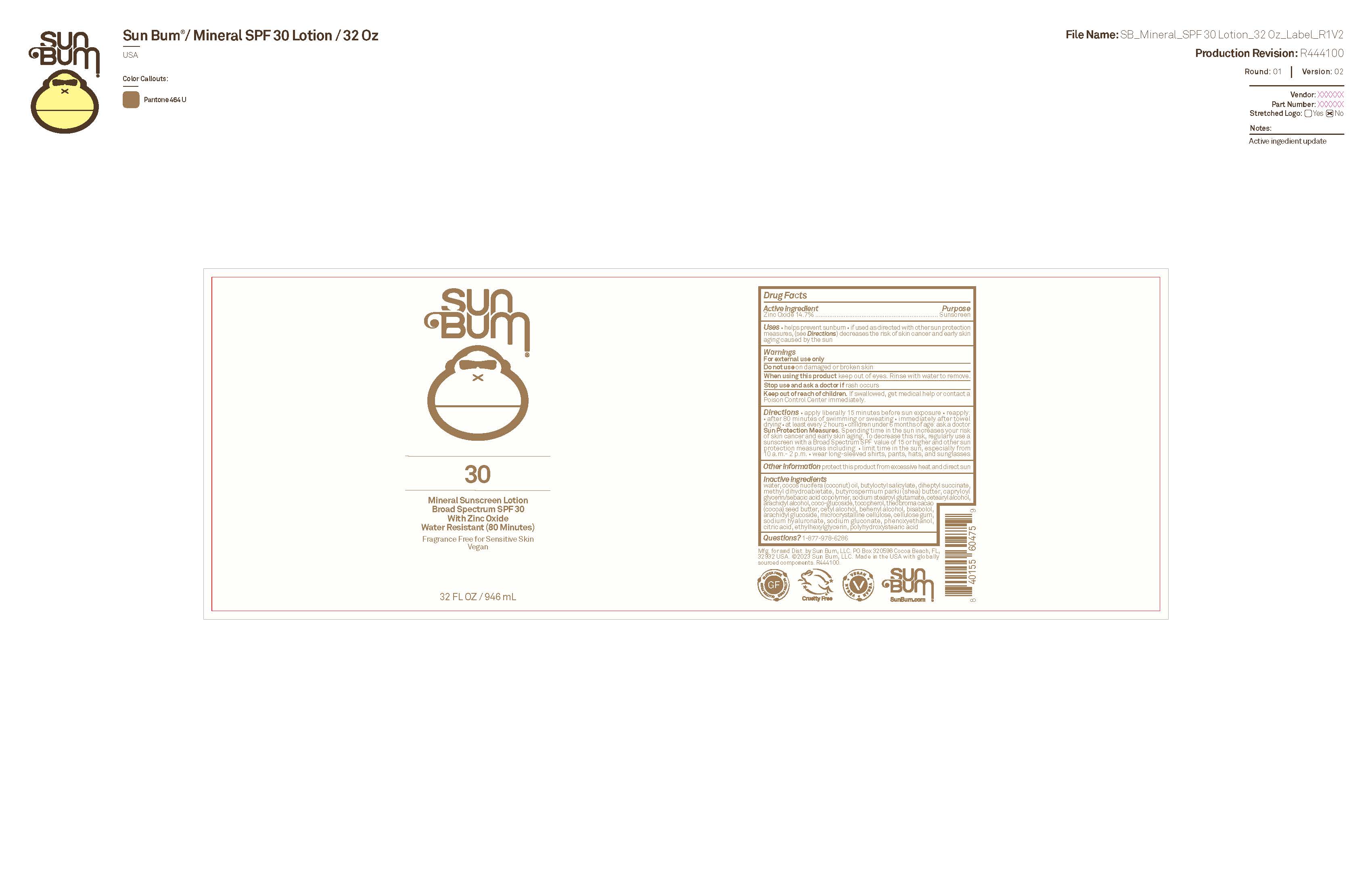 DRUG LABEL: Sun Bum 30 Mineral Sunscreen 32 OZ
NDC: 69039-764 | Form: LOTION
Manufacturer: Sun Bum, LLC
Category: otc | Type: HUMAN OTC DRUG LABEL
Date: 20250818

ACTIVE INGREDIENTS: ZINC OXIDE 147 mg/1 mL
INACTIVE INGREDIENTS: SODIUM STEAROYL GLUTAMATE; CAPRYLOYL GLYCERIN/SEBACIC ACID COPOLYMER (2000 MPA.S); TOCOPHEROL; METHYL DIHYDROABIETATE; ARACHIDYL ALCOHOL; CELLULOSE GUM; CETEARYL ALCOHOL; CETYL ALCOHOL; COCO-GLUCOSIDE; ARACHIDYL GLUCOSIDE; ETHYLHEXYLGLYCERIN; POLYHYDROXYSTEARIC ACID (2300 MW); BUTYLOCTYL SALICYLATE; BISABOLOL; MICROCRYSTALLINE CELLULOSE; PHENOXYETHANOL; CITRIC ACID; SODIUM HYALURONATE; DIHEPTYL SUCCINATE; BUTYROSPERMUM PARKII (SHEA) BUTTER; BEHENYL ALCOHOL; SODIUM GLUCONATE; WATER; COCOS NUCIFERA (COCONUT) OIL; THEOBROMA CACAO (COCOA) SEED BUTTER

Sun Bum 30 Mineral Sunscreen 32 OZ

Active Ingredients

Zinc Oxide 14.7%

Purpose

Sunscreen

Uses

• helps prevent sunburn • if used as directed with other sun protection measures, (see Directions) decreases the risk of skin cancer and early skin aging caused by the sun

Warnings

For external use only

Do not use on damaged or broken skin

When using this product keep out of eyes. Rinse with water to remove.

Stop use and ask a doctor if rash occurs

Keep out of reach of children. If swallowed, get medical help or contact a Poison Control Center immediately.

Warnings

Keep Out Of Reach Of Children

Directions

• apply liberally 15 minutes before sun exposure

• reapply: • after 80 minutes of swimming or sweating • immediately after towel drying • at least every 2 hours

• children under 6 months of age: ask a doctor

• Sun Protection Measures. Spending time in the sun increases your risk of skin cancer and early skin aging. To decrease this risk, regularly use a sunscreen with a Broad Spectrum SPF value of 15 or higher and other sun protection measures including:

• limit time in the sun, especially from 10 a.m.- 2 p.m.

• wear long-sleeved shirts, pants, hats and sunglasses

Directions

• apply liberally 15 minutes before sun exposure

Other Information

protect this product from excessive heat and direct sun

Inactive Ingredients

water, cocos nucifera (coconut) oil, butyloctyl salicylate, diheptyl succinate, methyl dihydroabietate, butyrospermum parkii (shea butter), capryloyl glycerin/sebacic acid copolymer, sodium stearoyl glutamate, cetearyl alcohol, arachidyl alcohol, coco-glucoside, tocopherol, theobroma cacao (cocoa) seed butter, cetyl alcohol, behenyl alcohol, bisabolol, arachidyl glucoside, microcrystalline cellulose, cellulose gum, sodium hyaluronate, sodium gluconate, phenoxyethanol, citric acid, ethylhexylglycerin, polyhydroxystearic acid

Questions?

1-877-978-6286